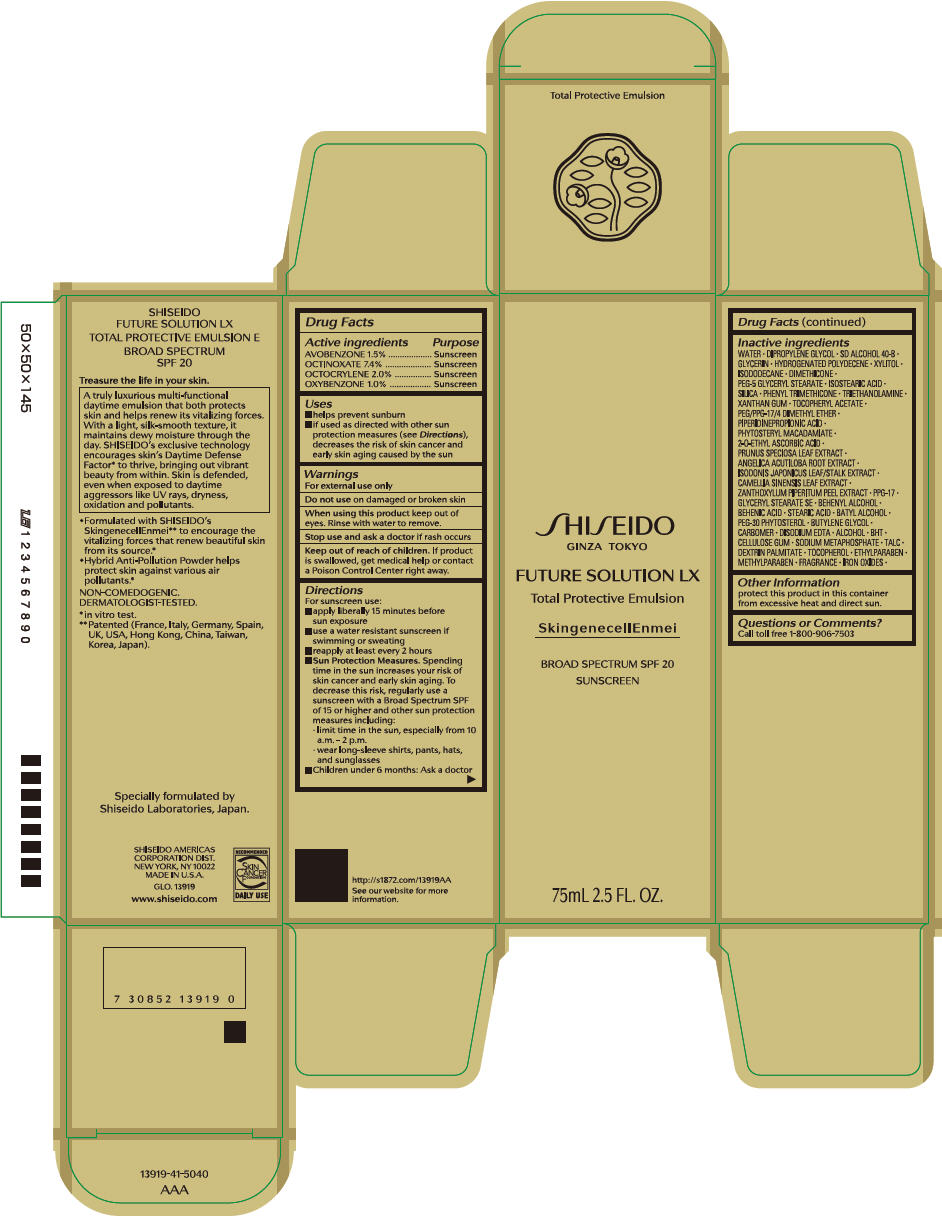 DRUG LABEL: Shiseido Future Solution LX Total Protective
NDC: 58411-327 | Form: EMULSION
Manufacturer: SHISEIDO AMERICAS CORPORATION
Category: otc | Type: HUMAN OTC DRUG LABEL
Date: 20260105

ACTIVE INGREDIENTS: AVOBENZONE 1136 mg/75 mL; OCTINOXATE 5606 mg/75 mL; OCTOCRYLENE 1515 mg/75 mL; OXYBENZONE 758 mg/75 mL
INACTIVE INGREDIENTS: PIPERIDINEPROPIONIC ACID; PHYTOSTERYL MACADAMIATE; 2-O-ETHYL ASCORBIC ACID; PRUNUS SPECIOSA LEAF; ANGELICA ACUTILOBA ROOT; GREEN TEA LEAF; ZANTHOXYLUM PIPERITUM FRUIT RIND; PPG-17; GLYCERYL MONOSTEARATE; DOCOSANOL; BEHENIC ACID; STEARIC ACID; BATILOL; BUTYLENE GLYCOL; CARBOMER HOMOPOLYMER, UNSPECIFIED TYPE; EDETATE DISODIUM; ALCOHOL; BUTYLATED HYDROXYTOLUENE; CARBOXYMETHYLCELLULOSE SODIUM, UNSPECIFIED; SODIUM POLYMETAPHOSPHATE; TALC; DEXTRIN PALMITATE (CORN; 20000 MW); .ALPHA.-TOCOPHEROL; ETHYLPARABEN; METHYLPARABEN; FERRIC OXIDE RED; FERRIC OXIDE YELLOW; WATER; DIPROPYLENE GLYCOL; GLYCERIN; HYDROGENATED POLYDECENE TYPE I; XYLITOL; ISODODECANE; DIMETHICONE; PEG-5 GLYCERYL STEARATE; ISOSTEARIC ACID; SILICON DIOXIDE; PHENYL TRIMETHICONE; TROLAMINE; XANTHAN GUM; .ALPHA.-TOCOPHEROL ACETATE, DL-; PEG/PPG-17/4 DIMETHYL ETHER

SHISEIDO FUTURE SOLUTION LX TOTAL PROTECTIVE

Drug Facts

ACTIVE INGREDIENT

Active ingredients | Purpose
AVOBENZONE 1.5% | Sunscreen
OCTINOXATE 7.4% | Sunscreen
OCTOCRYLENE 2.0% | Sunscreen
OXYBENZONE 1.0% | Sunscreen

Uses

- helps prevent sunburn
- if used as directed with other sun protection measures (see Directions), decreases the risk of skin cancer and early skin aging caused by the sun

Warnings

For external use only

Do not useon damaged or broken skin

WHEN USING

When using this productkeep out of eyes. Rinse with water to remove.

Stop use and ask a doctorif rash occurs

Keep out of reach of children.If product is swallowed, get medical help or contact a Poison Control Center right away.

Directions

For sunscreen use:

- apply liberally 15 minutes before sun exposure
- use a water resistant sunscreen if swimming or sweating
- reapply at least every 2 hours
- Sun Protection Measures. Spending time in the sun increases your risk of skin cancer and early skin aging. To decrease this risk, regularly use a sunscreen with a broad spectrum SPF of 15 or higher and other sun protection measures including:
  - limit time in the sun, especially from 10 a.m. – 2 p.m.
  - wear long-sleeve shirts, pants, hats, and sunglasses
- children under 6 months: Ask a doctor

Inactive Ingredients

WATER∙DIPROPYLENE GLYCOL∙SD ALCOHOL 40-B∙GLYCERIN∙HYDROGENATED POLYDECENE∙XYLITOL∙ISODODECANE∙DIMETHICONE∙PEG-5 GLYCERYL STEARATE∙ISOSTEARIC ACID∙SILICA∙PHENYL TRIMETHICONE∙TRIETHANOLAMINE∙XANTHAN GUM∙TOCOPHERYL ACETATE∙PEG/PPG-17/4 DIMETHYL ETHER∙PIPERIDINEPROPIONIC ACID∙PHYTOSTERYL MACADAMIATE∙2-O-ETHYL ASCORBIC ACID∙PRUNUS SPECIOSA LEAF EXTRACT∙ANGELICA ACUTILOBA ROOT EXTRACT∙ISODONIS JAPONICUS LEAF/STALK EXTRACT∙CAMELLIA SINENSIS LEAF EXTRACT∙ZANTHOXYLUM PIPERITUM PEEL EXTRACT∙PPG-17∙GLYCERYL STEARATE SE∙BEHENYL ALCOHOL∙BEHENIC ACID∙STEARIC ACID∙BATYL ALCOHOL∙PEG-30 PHYTOSTEROL∙BUTYLENE GLYCOL∙CARBOMER∙DISODIUM EDTA∙ALCOHOL∙BHT∙CELLULOSE GUM∙SODIUM METAPHOSPHATE∙TALC∙DEXTRIN PALMITATE∙TOCOPHEROL∙ETHYLPARABEN∙METHYLPARABEN∙FRAGRANCE∙IRON OXIDES∙

Other information

- protect this product in this container from excessive heat and direct sun.

Questions or comments?

Call toll free 1-800-906-7503

PRINCIPAL DISPLAY PANEL - 75 mL Bottle Carton

SHI SEIDO
GINZA TOKYO

FUTURE SOLUTION LX

Total Protective Emulsion

SkingenecellEnmei

BROAD SPECTRUM SPF 20
SUNSCREEN

75mL 2.5 FL. OZ.